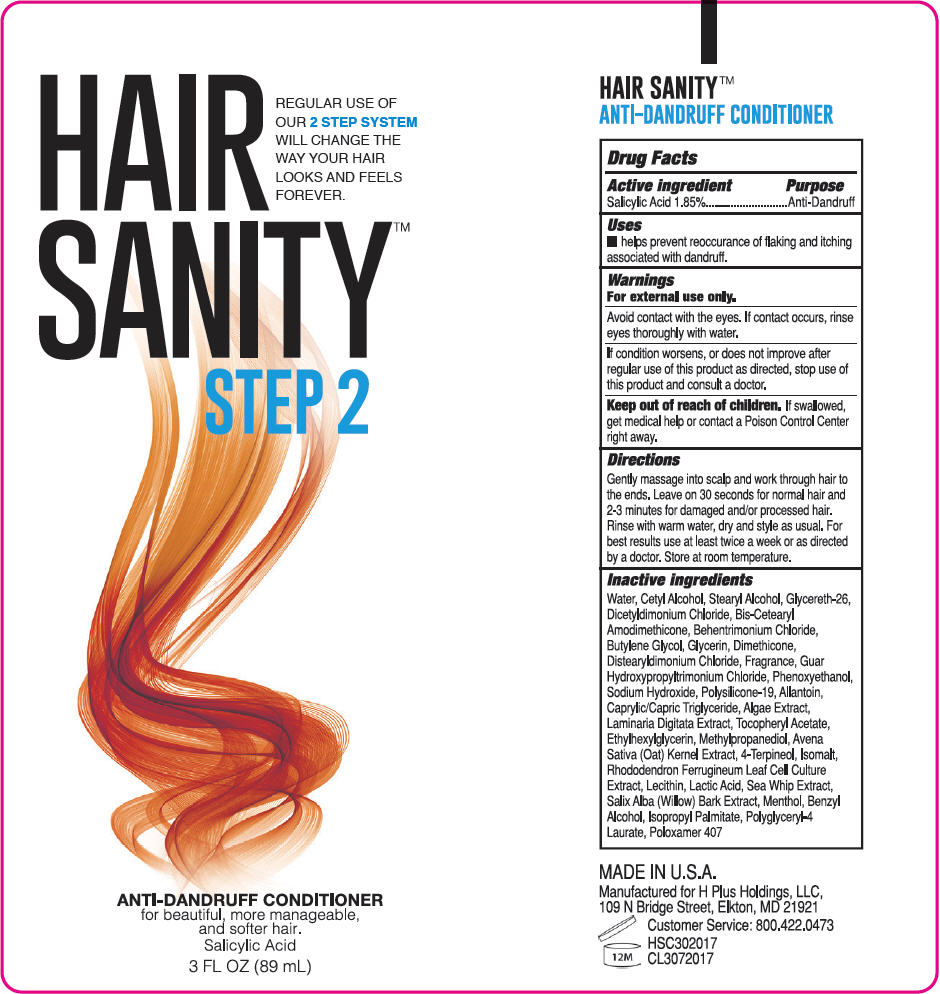 DRUG LABEL: HairSanity Step 2
NDC: 71605-100 | Form: LOTION/SHAMPOO
Manufacturer: H Plus Holdings
Category: otc | Type: HUMAN OTC DRUG LABEL
Date: 20170727

ACTIVE INGREDIENTS: Salicylic Acid 18.5 mg/1 mL
INACTIVE INGREDIENTS: CETYL ALCOHOL; STEARYL ALCOHOL; GLYCERETH-26; DICETYLDIMONIUM CHLORIDE; BEHENTRIMONIUM CHLORIDE; BUTYLENE GLYCOL; GLYCERIN; DIMETHICONE; DISTEARYLDIMONIUM CHLORIDE; GUAR HYDROXYPROPYLTRIMONIUM CHLORIDE (1.7 SUBSTITUENTS PER SACCHARIDE); PHENOXYETHANOL; SODIUM HYDROXIDE; MEDIUM-CHAIN TRIGLYCERIDES; .ALPHA.-TOCOPHEROL ACETATE; ALLANTOIN; ETHYLHEXYLGLYCERIN; METHYLPROPANEDIOL; OAT; 4-TERPINEOL, (+)-; LECITHIN, SOYBEAN; ISOPROPYL PALMITATE; POLOXAMER 407; ISOMALT; PSEUDOPTEROGORGIA ELISABETHAE; PHYMATOLITHON CALCAREUM; SALIX ALBA BARK; MENTHOL, UNSPECIFIED FORM; BENZYL ALCOHOL; LAMINARIA DIGITATA; RHODODENDRON FERRUGINEUM LEAF; LACTIC ACID, UNSPECIFIED FORM; WATER

HairSanity™ Step 2

Drug Facts

Active ingredient

Salicylic Acid 1.85%

Purpose

Anti-Dandruff

Uses

- helps prevent reoccurance of flaking and itching associated with dandruff.

Warnings

For external use only.

Avoid contact with the eyes. If contact occurs, rinse eyes thoroughly with water.

STOP USE

If condition worsens, or does not improve after regular use of this product as directed, stop use of this product and consult a doctor.

Keep out of reach of children. If swallowed, get medical help or contact a Poison Control Center right away.

Directions

Gently massage into scalp and work through hair to the ends. Leave on 30 seconds for normal hair and 2-3 minutes for damaged and/or processed hair. Rinse with warm water, dry and style as usual. For best results use at least twice a week or as directed by a doctor. Store at room temperature.

Inactive ingredients

Water, Cetyl Alcohol, Stearyl Alcohol, Glycereth-26, Dicetyldimonium Chloride, Bis-Cetearyl Amodimethicone, Behentrimonium Chloride, Butylene Glycol, Glycerin, Dimethicone, Distearyldimonium Chloride, Fragrance, Guar Hydroxypropyltrimonium Chloride, Phenoxyethanol, Sodium Hydroxide, Polysilicone-19, Allantoin, Caprylic/Capric Triglyceride, Algae Extract, Laminaria Digitata Extract, Tocopheryl Acetate, Ethylhexylglycerin, Methylpropanediol, Avena Sativa (Oat) Kernel Extract, 4-Terpineol, Isomalt, Rhododendron Ferrugineum Leaf Cell Culture Extract, Lecithin, Lactic Acid, Sea Whip Extract, Salix Alba (Willow) Bark Extract, Menthol, Benzyl Alcohol, Isopropyl Palmitate, Polyglyceryl-4 Laurate, Poloxamer 407

PRINCIPAL DISPLAY PANEL - 89 mL Tube Label

HAIR
SANITY™
STEP 2

REGULAR USE OF
OUR 2 STEP SYSTEM
WILL CHANGE THE
WAY YOUR HAIR
LOOKS AND FEELS
FOREVER.

ANTI-DANDRUFF CONDITIONER
for beautiful, more manageable,
and softer hair.
Salicylic Acid

3 FL OZ (89 mL)